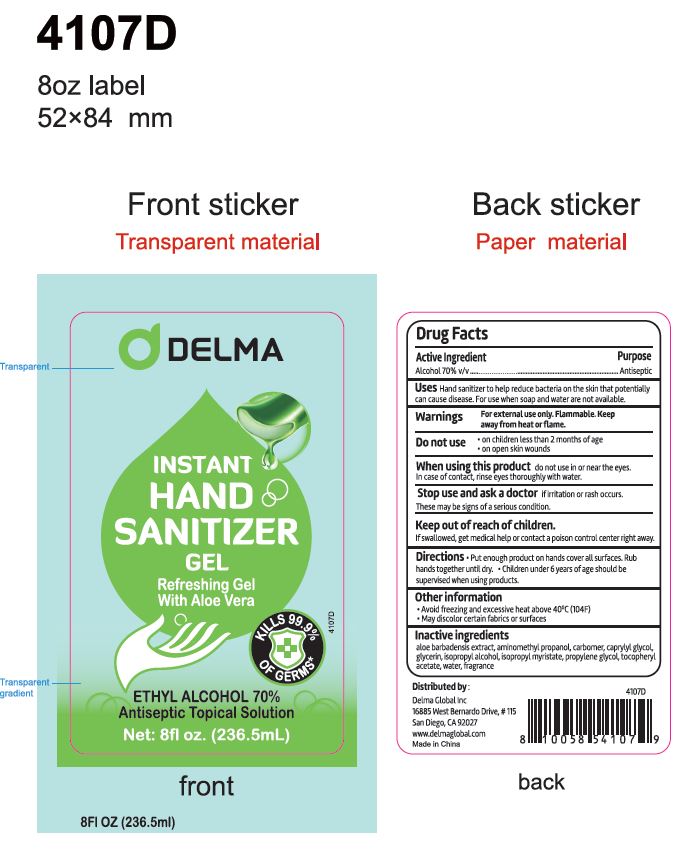 DRUG LABEL: Delma
NDC: 80208-112 | Form: GEL
Manufacturer: Delma Global, Inc
Category: otc | Type: HUMAN OTC DRUG LABEL
Date: 20220114

ACTIVE INGREDIENTS: ALCOHOL 70 mL/100 mL
INACTIVE INGREDIENTS: ISOPROPYL ALCOHOL; GLYCERIN; ALOE VERA LEAF; WATER; PROPYLENE GLYCOL; AMINOMETHYLPROPANOL; CARBOMER HOMOPOLYMER, UNSPECIFIED TYPE; CAPRYLYL GLYCOL; ISOPROPYL MYRISTATE; .ALPHA.-TOCOPHEROL ACETATE; FRAGRANCE LEMON ORC2001060

Delma Hand Sanitizer with Fragrance

Active Ingredient(s)

Alcohol 70% v/v. Purpose: Antiseptic

Purpose

Antiseptic, Hand Sanitizer

Use

Hand Sanitizer to help reduce bacteria that potentially can cause disease. For use when a soap and water are not available.

Warnings

For external use only. Flammable. Keep away from heat or flame

Do not use

- in children less than 2 months of age
- on open skin wounds

When using this product keep out of eyes, ears, and mouth. In case of contact with eyes, rinse eyes thoroughly with water.
Stop use and ask a doctor if irritation or rash occurs. These may be signs of a serious condition.
Keep out of reach of children. If swallowed, get medical help or contact a Poison Control Center right away.

Stop use and ask a doctor if irritation or rash occurs. These may be signs of a serious condition.

Keep out of reach of children. If swallowed, get medical help or contact a Poison Control Center right away.

Directions

- Place enough product on hands to cover all surfaces. Rub hands together until dry.
- Supervise children under 6 years of age when using this product to avoid swallowing.

Other information

Avoid freezing and excessive heat above the 40C (104 F)

May discolor certain fabrics or surfaces

Inactive ingredients

aloe barbadensis extract, aminomethyl propanol, carbomer, caprylyl glycol, glycerin, isopropyl alcohol, isopropyl myristate, propylene glycol, tocopheryl acetate, water

Package Label - Principal Display Panel

236 mL NDC: 80208-112-03